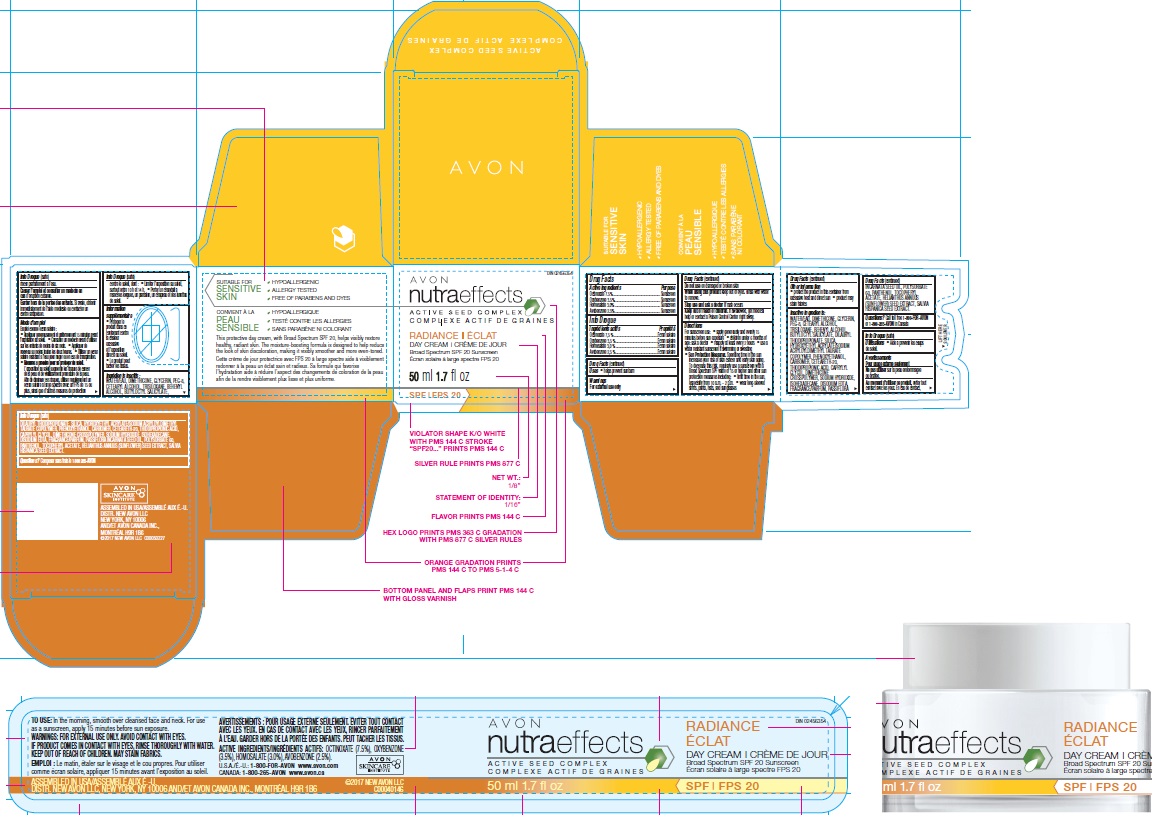 DRUG LABEL: Nutra Effects Radiance Day Cream SPF20
NDC: 10096-9500 | Form: CREAM
Manufacturer: New Avon LLC
Category: otc | Type: HUMAN OTC DRUG LABEL
Date: 20180326

ACTIVE INGREDIENTS: OCTINOXATE 7.5 g/100 g; OXYBENZONE 3.5 g/100 g; HOMOSALATE 3 g/100 g; AVOBENZONE 2.5 g/100 g
INACTIVE INGREDIENTS: WATER

Nutra Effects Radiance Day Cream SPF20

ACTIVE INGREDIENT

Active Ingredients/Ingrédients actifs:

OCTINOXATE (7.5 %), OXYBENZONE (3.5 %), HOMOSALATE (3.0 %), AVOBENZONE (2.5 %).

INDICATIONS & USAGE

Uses

- helps prevent sunburn

WARNINGS

For external use only

Do not use on damaged or broken skin

When using this product keep out of eyes. Rinse with water to remove.

Stop use and ask a doctor if rash occurs

Keep out of reach of children. If swallowed, get medical help or contact a Poison Control Center right away.

DOSAGE & ADMINISTRATION

Directions

- For sunscreen use:
- apply generously and evenly 15 minutes before sun exposure
- children under 6 months of age: ask a doctor
- reapply at least every 2 hours
- use a water resistant sunscreen if swimming or sweating

Sun Protection Measures. Spending time in the sun increases your risk of skin cancer and early skin aging. To decrease this risk, regularly use a sunscreen with a Broad Spectrum SPF value of 15 or higher and other sun protection measures including:

- limit time in the sun, especially from 10 a.m. – 2 p.m.
- wear long-sleeved shirts, pants, hats, and sunglasses

Other Information

- protect the product in this container from excessive heat and direct sun
- product may stain fabrics

INACTIVE INGREDIENT

Inactive Ingredients/Ingrédients inactifs: WATER/EAU, DIMETHICONE, GLYCERIN, PEG-8, CETEARYL ALCOHOL, TRISILOXANE, BEHENYL ALCOHOL, BUTYLOCTYL SALICYLATE, DILAURYL THIODIPROPIONATE, SILICA, HYDROXYETHYL ACRYLATE/SODIUM ACRYLOYLDIMETHYL TAURATE COPOLYMER, PHENOXYETHANOL, CARBOMER, CETEARETH-20, THIODIPROPIONIC ACID, CAPRYLYL GLYCOL, DIMETHICONE CROSSPOLYMER, SODIUM HYDROXIDE, ISOHEXADECANE, DISODIUM EDTA, FRAGRANCE/PARFUM, PASSIFLORA INCARNATA SEED OIL, POLYSORBATE 60, PANTHENOL, TOCOPHERYL ACETATE, HELIANTHUS ANNUUS (SUNFLOWER) SEED EXTRACT, SALVIA HISPANICA SEED EXTRACT.

QUESTIONS

Questions or Comments?
Call toll free 1-800-FOR-AVON or 1-800-265-AVON in Canada